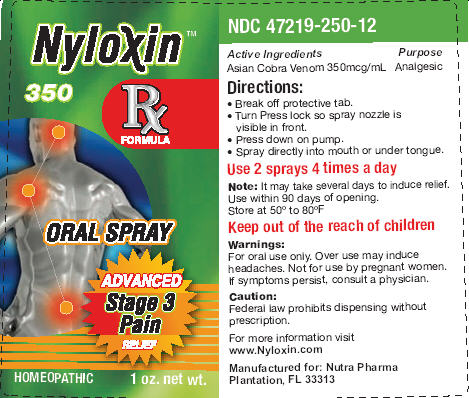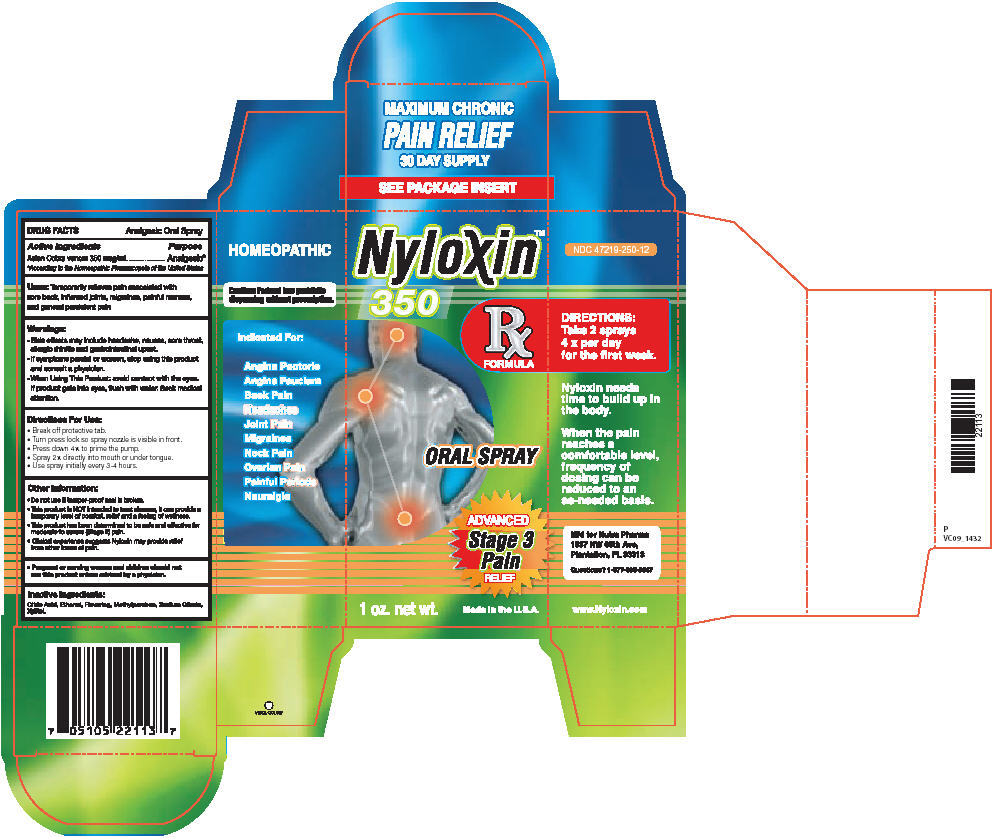 DRUG LABEL: NYLOXIN
NDC: 47219-252 | Form: SPRAY, METERED
Manufacturer: RECEPTOPHARM INC
Category: homeopathic | Type: HUMAN OTC DRUG LABEL
Date: 20091130

ACTIVE INGREDIENTS: NAJA NAJA VENOM 350 ug/1 mL
INACTIVE INGREDIENTS: ANHYDROUS CITRIC ACID; ANHYDROUS TRISODIUM CITRATE; METHYLPARABEN; XYLITOL; 2-(DIETHYLAMINO)ETHANOL

DRUG FACTS

Active Ingredients

Asian Cobra venom 350 mcg/mL

Purpose

Analgesic [According to the Homeopathic Pharmacopeia of the United States]

INDICATIONS AND USAGE

Uses: Temporarily relieves pain associated with sore back, inflamed joints, migraines, painful menses, and general presistent pain

Warnings:

- Side effects may include headahce, nausea, sore throat, allergic rhinitis and gastointestinal upset.
- If symptoms persist or worsen, stop using this product and consult a physician.
- When Using This Product: avoid contact with the eyes. If product gets into eyes, flush with water. Seek medical attention.

Directions For Use:

- Break off protective tab.
- Turn press lock so spray nozzle is visible in front.
- Press down 4 x to prime the pump.
- Spray 2 x directly into mouth or under tongue.
- Use spray intially every 3-4 hours.

Other Information:

- Do not use if tamper-proof seal is broken.
- This product is NOT intended to treat disease, it can provide a temporary level of comfort, relief and a feeling of wellness.
- This product has been determined to be safe and effective for moderate to severe (Stage 2) pain.
- Clinical experience suggests Nyloxin may provide relief from other forms of pain.

- Pregnant or nursing women and children should not use this product unless advised by a physician.

Inactive Ingredients:

Citric Acid, Ethanol, Flavoring, Methylparaben, Sodium Citrate, Xylitol.

PACKAGE LABEL

Package Label - Principal Display Panel – 1.0 oz Spray Label

PACKAGE LABEL

Package Label - Principal Display Panel – 1.0 oz Spray Carton